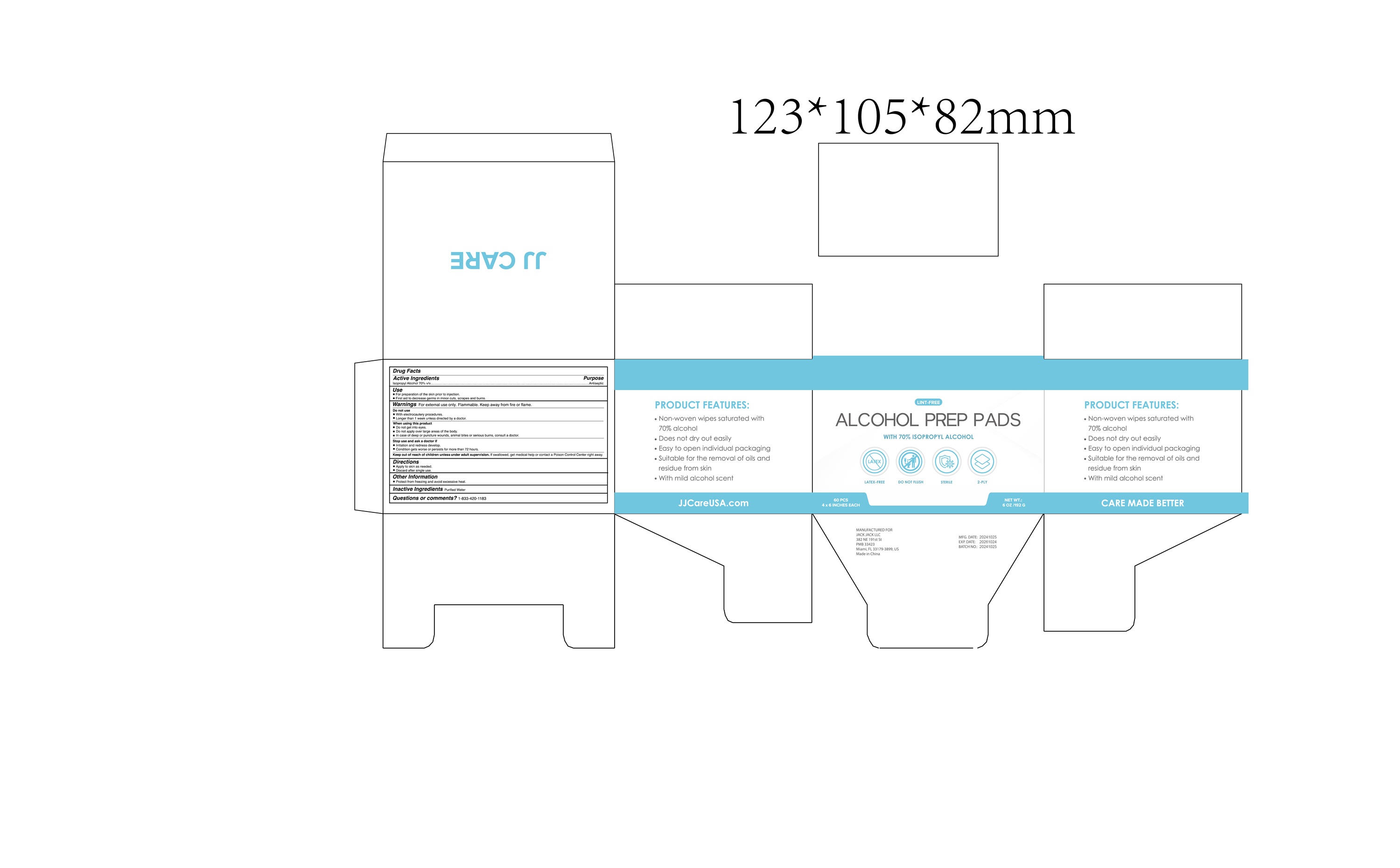 DRUG LABEL: Alcohol prep pads
NDC: 85361-003 | Form: CLOTH
Manufacturer: SHAOXING KEQIAO HUNIAN HEALTH PRODUCTS CO.,LTD
Category: otc | Type: HUMAN OTC DRUG LABEL
Date: 20250805

ACTIVE INGREDIENTS: ISOPROPYL ALCOHOL 0.7 mL/1 mL
INACTIVE INGREDIENTS: WATER

Active Ingredients

- ISOPROPYL ALCOHOL 70% v/v

Indications for use

- For preparation of the skin prior to injection.

- First aid to decrease germs in minor cuts, scrapes and burns.

Warnings

- For external use only. Flammable. Keep away from fire or flame.

Do not use

- With clectrocautery procedures.

- Longer than 1 week unless directed by a doctor.

When using this product

- Do not get into eyes

- Do not apply over large areas of the body

- In case of deep or puncture wounds, animals bites or serious burns, consult a doctor.

Stop use and ask a doctor if

- irritation and redness develop

- Condition gets worse or persists for more than 72 hours

Keep out of reach of children unless adult supervision

- if swallowed, get medical help or contact a Posion Control Center right away.

Directions

- Apply to skin as needed

- Diccard after single use

Other information

- avoid freezing and excessive heat

Inactive Ingredients

- Purified Water

Questions or Comments

- 1-833-420-1183

Purpose

- for preparation of the skin prior to injection

- first aid to decrease germs in minor outs, scrapes and burns

Dosage & Administration

- 1-2 pieces